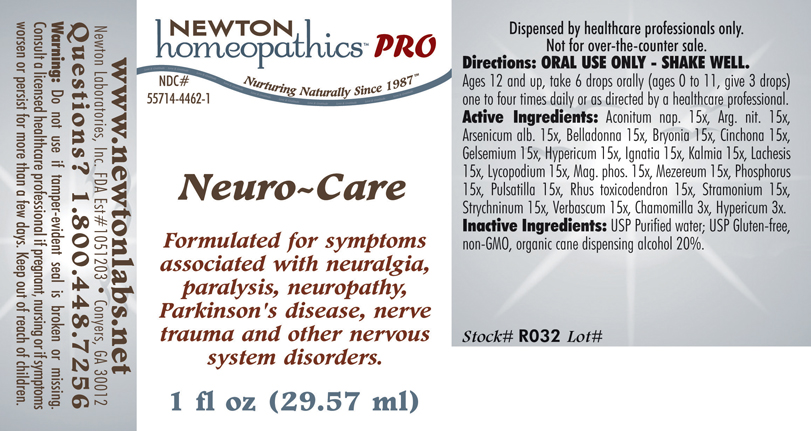 DRUG LABEL: Neuro - Care 
NDC: 55714-4462 | Form: LIQUID
Manufacturer: Newton Laboratories, Inc.
Category: homeopathic | Type: HUMAN PRESCRIPTION DRUG LABEL
Date: 20110601

ACTIVE INGREDIENTS: Aconitum Napellus 15 [hp_X]/1 mL; Silver Nitrate 15 [hp_X]/1 mL; Arsenic Trioxide 15 [hp_X]/1 mL; Atropa Belladonna 15 [hp_X]/1 mL; Bryonia Alba Root 15 [hp_X]/1 mL; Cinchona Officinalis Bark 15 [hp_X]/1 mL; Gelsemium Sempervirens Root 15 [hp_X]/1 mL; Hypericum Perforatum 15 [hp_X]/1 mL; Strychnos Ignatii Seed 15 [hp_X]/1 mL; Kalmia Latifolia Leaf 15 [hp_X]/1 mL; Lachesis Muta Venom 15 [hp_X]/1 mL; Lycopodium Clavatum Spore 15 [hp_X]/1 mL; Magnesium Phosphate, Dibasic Trihydrate 15 [hp_X]/1 mL; Daphne Mezereum Bark 15 [hp_X]/1 mL; Phosphorus 15 [hp_X]/1 mL; Pulsatilla Vulgaris 15 [hp_X]/1 mL; Toxicodendron Pubescens Leaf 15 [hp_X]/1 mL; Datura Stramonium 15 [hp_X]/1 mL; Strychnine 15 [hp_X]/1 mL; Verbascum Thapsus 15 [hp_X]/1 mL; Matricaria Recutita 3 [hp_X]/1 mL
INACTIVE INGREDIENTS: Alcohol

Neuro - Care

INDICATIONS & USAGE SECTION

Neuro - Care Formulated for symptoms associated with neuralgia, paralysis, neuropathy, Parkinson's disease, nerve trauma and other nervous system disorders.

DOSAGE & ADMINISTRATION SECTION

Directions: ORAL USE ONLY - SHAKE WELL. Ages 12 and up, take 6 drops orally (ages 0 to 11, give 3 drops) one to four times daily or as directed by a healthcare professional.

ACTIVE INGREDIENT SECTION

Aconitum nap. 15x, Arg. nit. 15x, Arsenicum alb. 15x, Belladonna 15x, Bryonia 15x, Cinchona 15x, Gelsemium 15x, Hypericum 15x, Ignatia 15x, Kalmia 15x, Lachesis 15x, Lycopodium 15x, Mag. phos. 15x, Mezereum 15x, Phosphorus 15x, Pulsatilla 15x, Rhus toxicodendron 15x, Stramonium 15x, Strychninum 15x, Verbascum 15x, Chamomilla 3x, Hypericum 3x.

PURPOSE SECTION

Formulated for symptoms associated with neuralgia, paralysis, neuropathy, Parkinson's disease, nerve trauma and other nervous system disorders.

INACTIVE INGREDIENT SECTION

Inactive Ingredients: USP Purified Water; USP Gluten-free, non-GMO, organic cane dispensing alcohol 20%.

QUESTIONS? SECTION

www.newtonlabs.net Newton Laboratories, Inc. FDA Est # 1051203 - Conyers, GA 30012
Questions? 1.800.448.7256

WARNINGS SECTION

Warning: Do not use if tamper - evident seal is broken or missing. Consult a licensed healthcare professional if pregnant, nursing or if symptoms worsen or persist for more than a few days. Keep out of reach of children.

PREGNANCY OR BREAST FEEDING SECTION

Consult a licensed healthcare professional if pregnant, nursing or if symptoms worsen or persist for more than a few days.

KEEP OUT OF REACH OF CHILDREN SECTION

Keep out of reach of children.